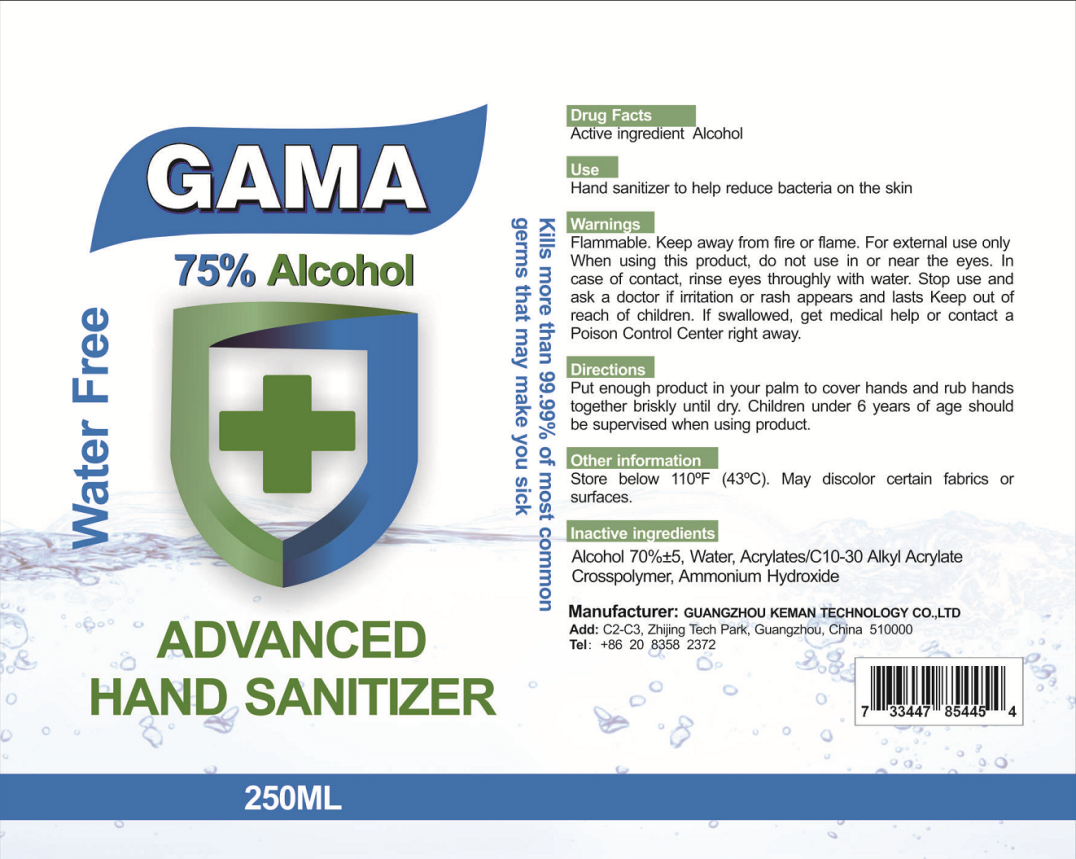 DRUG LABEL: Hand Sanitizer
NDC: 55866-008 | Form: GEL
Manufacturer: Guangzhou Keman Technology Co., Ltd.
Category: otc | Type: HUMAN OTC DRUG LABEL
Date: 20200807

ACTIVE INGREDIENTS: ALCOHOL 187.5 mL/250 mL
INACTIVE INGREDIENTS: WATER; AMMONIA; CARBOMER INTERPOLYMER TYPE A (55000 CPS)

DOSAGE AND ADMINISTRATION

Store below 110°F (43°C).

INACTIVE INGREDIENT

Water，Acrylates/C10-30 Alkyl Acrylate Crosspolymer, Ammonium Hydroxide

INDICATIONS AND USAGE

Put enough product in your palm to cover hands and rub hands together briskly until dry.

ACTIVE INGREDIENT

Ethanol

keep out of reach of children

PURPOSE

Disinfection
Sterilization

WARNINGS

Flammable. Keep away from fire or flame. For extermal use only When using this product, do not use in or near the eyes. In case of contact, rinse eyes throughly with water. Stop use and ask a doctor if iritation or rash appears and lasts Keep out of reach of children. If swallowed, get medical help or contact a Poison Control Center right away.